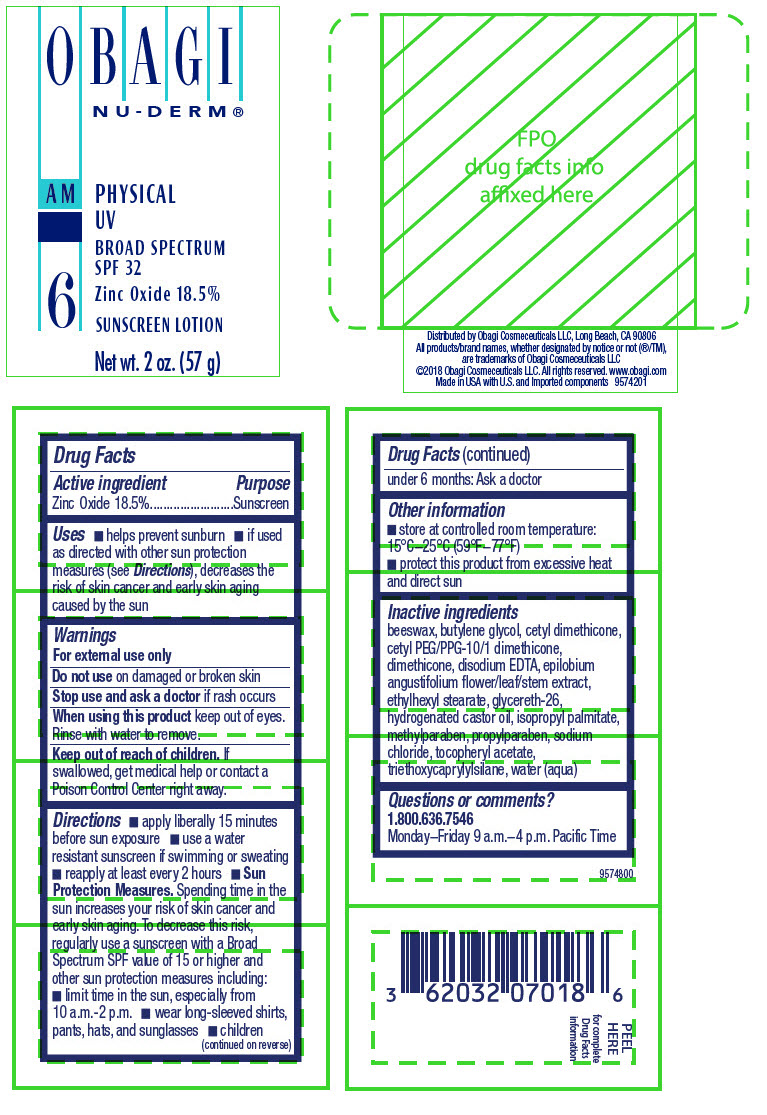 DRUG LABEL: NU-DERM PHYSICAL UV
NDC: 62032-070 | Form: LOTION
Manufacturer: Obagi Cosmeceuticals LLC
Category: otc | Type: HUMAN OTC DRUG LABEL
Date: 20190117

ACTIVE INGREDIENTS: ZINC OXIDE 185 mg/1 g
INACTIVE INGREDIENTS: ISOPROPYL PALMITATE; WATER; ETHYLHEXYL STEARATE; HYDROGENATED CASTOR OIL; YELLOW WAX; GLYCERETH-26; SODIUM CHLORIDE; METHYLPARABEN; DIMETHICONE; PROPYLPARABEN; EDETATE DISODIUM; EPILOBIUM ANGUSTIFOLIUM FLOWERING TOP; CETYL PEG/PPG-10/1 DIMETHICONE (HLB 5); BUTYLENE GLYCOL; .ALPHA.-TOCOPHEROL ACETATE; TRIETHOXYCAPRYLYLSILANE

OBAGI
NU-DERM®
AM
PHYSICAL
UV
BROAD SPECTRUM
SPF 32
SUNSCREEN LOTION

Drug Facts

ACTIVE INGREDIENT

Active ingredient | Purpose
Zinc Oxide 18.5% | Sunscreen

Uses

- helps prevent sunburn
- if used as directed with other sun protection measures (see Directions), decreases the risk of skin cancer and early skin aging caused by the sun

Warnings

- For external use only
- Do not use on damaged or broken skin
- Stop use and ask a doctor if rash occurs
- When using this product keep out of eyes. Rinse with water to remove.
- Keep out of reach of children. If swallowed, get medical help or contact a Poison Control Center right away.

Directions

- apply liberally 15 minutes before sun exposure
- use a water resistant sunscreen if swimming or sweating
- reapply at least every 2 hours
- children under 6 months: Ask a doctor
- Sun Protection Measures. Spending time in the sun increases your risk of skin cancer and early skin aging. To decrease this risk, regularly use a sunscreen with a Broad Spectrum SPF value of 15 or higher and other sun protection measures including:
  - limit time in the sun, especially from 10 a.m.-2 p.m.
  - wear long-sleeved shirts, pants, hats, and sunglasses

Inactive ingredients

beeswax, butylene glycol, cetyl dimethicone, cetyl PEG/PPG-10/1 dimethicone, dimethicone, disodium EDTA, epilobium angustifolium flower/leaf/stem extract, ethylhexyl stearate, glycereth-26, hydrogenated castor oil, isopropyl palmitate, methylparaben, propylparaben, sodium chloride, tocopherol acetate, triethoxycaprylylsilane, water

Other information

- store at controlled room temperature: 15°C-25°C (59°F-77°F)
- protect this product from excessive heat and direct sun

Questions or comments?

1.800.636.7546
Monday-Friday 9 a.m.-4 p.m. Pacific Time

Obagi Nu-Derm is a registered trademark of OMP, Inc.

Distributed by OMP, Inc., Long Beach, CA 90806

©2012 Obagi Medical Products, Inc. All rights reserved.

www.obagi.com
Made in USA

10701810Z 7018

PRINCIPAL DISPLAY PANEL - 57 g Bottle Label

OBAGI
NU-DERM®

AM
PHYSICAL
UV
BROAD SPECTRUM
SPF 32

6

Zinc Oxide 18.5%

SUNSCREEN LOTION

Net wt. 2 oz. (57 g)